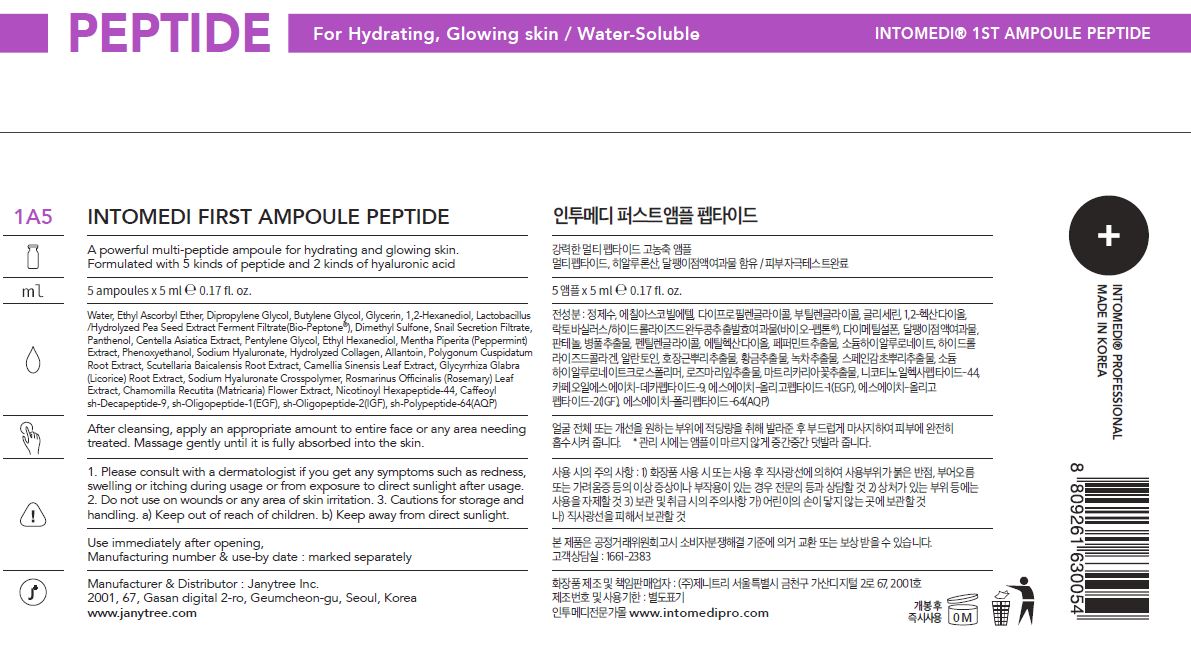 DRUG LABEL: INTOMEDI FIRST AMPOULE PEPTIDE
NDC: 82879-0006 | Form: LIQUID
Manufacturer: Janytree Inc.
Category: otc | Type: HUMAN OTC DRUG LABEL
Date: 20220712

ACTIVE INGREDIENTS: HYALURONATE SODIUM 0.5 g/100 mL
INACTIVE INGREDIENTS: BUTYLENE GLYCOL; WATER; GLYCERIN

INACTIVE INGREDIENTS

Water, Ethyl Ascorbyl Ether, Dipropylene Glycol, Butylene Glycol, Glycerin, 1,2-Hexanediol, Lactobacillus
/Hydrolyzed Pea Seed Extract Ferment Filtrate(Bio-Peptone®), Dimethyl Sulfone, Snail Secretion Filtrate,
Panthenol, Centella Asiatica Extract, Pentylene Glycol, Ethyl Hexanediol, Mentha Piperita (Peppermint)
Extract, Phenoxyethanol, Hydrolyzed Collagen, Allantoin, Polygonum Cuspidatum
Root Extract, Scutellaria Baicalensis Root Extract, Camellia Sinensis Leaf Extract, Glycyrrhiza Glabra
(Licorice) Root Extract, Sodium Hyaluronate Crosspolymer, Rosmarinus Officinalis (Rosemary) Leaf
Extract, Chamomilla Recutita (Matricaria) Flower Extract, Nicotinoyl Hexapeptide-44, Caffeoyl
sh-Decapeptide-9, sh-Oligopeptide-1(EGF), sh-Oligopeptide-2(IGF), sh-Polypeptide-64(AQP)

ACTIVE INGREDIENTS

Sodium Hyaluronate

PURPOSE

A powerful multi-peptide ampoule for hydrating and glowing skin.
Formulated with 5 kinds of peptide and 2 kinds of hyaluronic acid

WARNINGS

For external use only When using this product
■ If following abnormal symptoms occurs after using the product, stop using the product and consult with a skin specialist. Symptoms : Red specks, swelling, itching
■ Do not use on the skin parts affected by wound, eczema, or dermatitis.
Keep out of reach of children.
■ If swallowed, get a medical help or contact a person in control center immediately.
■ Avoid contact with eyes.

KEEP OUT OF REACH OF CHILDREN

If swallowed, get a medical help or contact a person in control center immediately.

INDICATIONS AND USAGE

After cleansing, apply an appropriate amount to entire face or any area needing
treated. Massage gently until it is fully absorbed into the skin.

DOSAGE AND ADMINISTRATION

for external use only